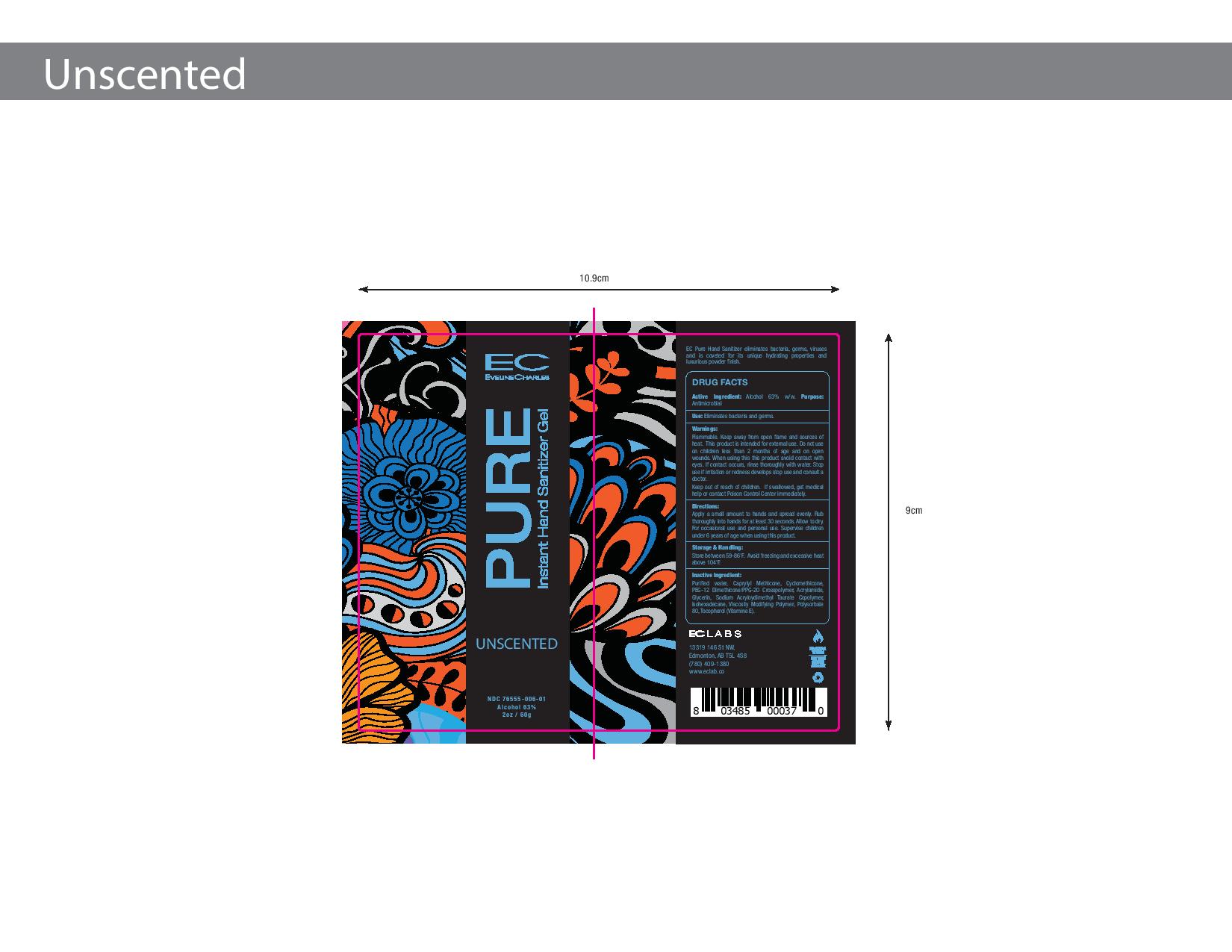 DRUG LABEL: EC Pure Instant Cream Hand Sanitizer Unscented
NDC: 76555-006 | Form: CREAM
Manufacturer: Ec Labs Inc.
Category: otc | Type: HUMAN OTC DRUG LABEL
Date: 20220114

ACTIVE INGREDIENTS: ALCOHOL 37.8 g/60 g
INACTIVE INGREDIENTS: GLYCERIN 0.3 g/60 g; TOCOPHEROL 0.06 g/60 g; WATER 13.2 g/60 g; PEG/PPG-18/12 DIMETHICONE 5.1 g/60 g; AMMONIUM ACRYLOYLDIMETHYLTAURATE, DIMETHYLACRYLAMIDE, LAURYL METHACRYLATE AND LAURETH-4 METHACRYLATE COPOLYMER, TRIMETHYLOLPROPANE TRIACRYLATE CROSSLINKED (45000 MPA.S) 0.78 g/60 g; CYCLOMETHICONE 1.02 g/60 g; SODIUM ACRYLOYLDIMETHYLTAURATE 1.74 g/60 g

Eveline Charles Pure Instant Cream Hand Sanitizer Unscented

This is a hand sanitizer manufactured according to the Temporary Policy for Preparation of Certain Alcohol-Based Hand Sanitizer Products During the Public Health Emergency (CoViD-19); Guidance for Industry.

The hand sanitizer is manufactured using only the following United States Pharmacopoeia (USP) grade ingredients in the preparation of the product (percentage in final product formulation) consistent with World Health Organization (WHO) recommendations:

1. Alcohol (ethanol) (USP or Food Chemical Codex (FCC) grade) (80%, volume/volume (v/v)) in an aqueous solution denatured according to Alcohol and Tobacco Tax and Trade Bureau regulations in 27 CFR part 20.
2. Glycerol (1.45% v/v).
3. Hydrogen peroxide (0.125% v/v).
4. Sterile distilled water or boiled cold water.

The firm does not add other active or inactive ingredients. Different or additional ingredients may impact the quality and potency of the product.

Active Ingredient(s)

Alcohol 63% w/w Purpose: Antimicrobial

Use

Eliminates bacteria and germs.

Warnings

Flammable. Keep away from open flame and sources of heat. This product is intended for external use only.

Do not use on children less than 2 months of age and on open wounds.

When using this product avoid contact with eyes. If contact occurs, rinse eyes thoroughly with water.

Stop use if irritation or redness occurs and consult a doctor.

Keep out of reach of children. If swallowed, get medical help or contact a Poison Control Center right away.

Directions

Apply a small amount to hands and spread evenly.

Rub thoroughly into hands for at least 30 seconds.

Allow to dry.

For occasional and personal use.

Supervise children under 6 years of age when using this product.

Other information

- Store between 59-86F
- Avoid freezing and excessive heat above 104F

Inactive ingredients

glycerin, hydrogen peroxide, purified water USP

Purpose

Antimicrobial. Hand sanitizer.

Package Label - Principal Display Panel

60g NDC: 76555-006-01